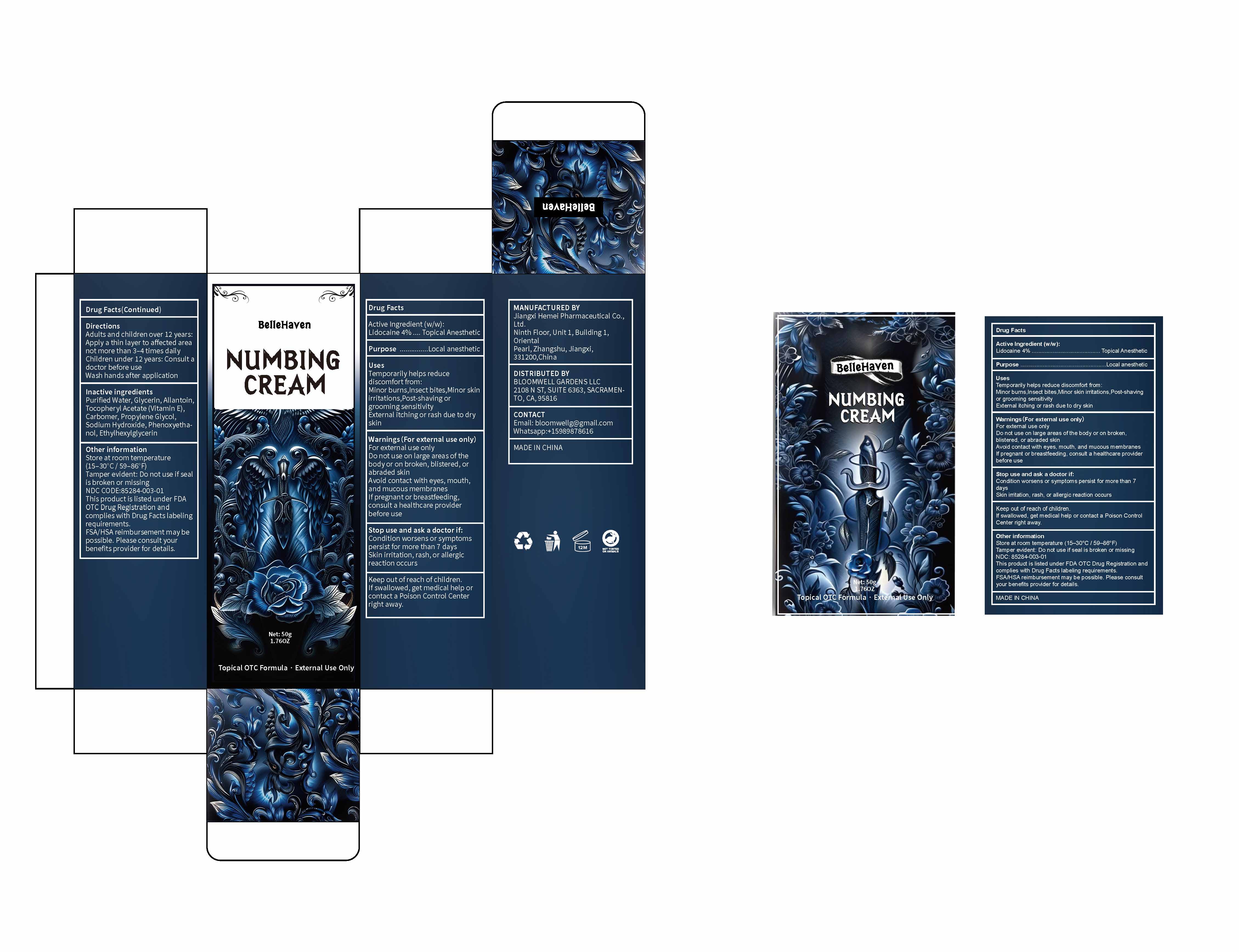 DRUG LABEL: Numbing Cream
NDC: 85284-003 | Form: CREAM
Manufacturer: BLOOMWELL GARDENS LLC
Category: otc | Type: HUMAN OTC DRUG LABEL
Date: 20250625

ACTIVE INGREDIENTS: LIDOCAINE 4 g/100 g
INACTIVE INGREDIENTS: WATER; GLYCERIN; ALPHA-TOCOPHEROL ACETATE; CARBOMER; SODIUM HYDROXIDE; PHENOXYETHANOL; PROPYLENE GLYCOL; ALLANTOIN; ETHYLHEXYLGLYCERIN

ACTIVE INGREDIENT

Lidocaine 4% ---Topical anesthetic

PURPOSE

Local anesthetic

USES

Temporarily helps reduce discomfort from:

Minor burns,Insect bites,Minor skin,irritations,Post-shaving or grooming sensitivity.

External itching or rash due to dry skin.

WARNINGS

For external use only

Do not use on large areas of the body or on broken, blistered, or abraded skin.

Avoid contact with eyes, mouth, and mucous membranes.

If pregnant or breastfeeding, consult a healthcare provider before use.

Stop use and ask a doctor if:

Condition worsens or symptomspersist for more than 7 days.

Skin irritation, rash, or allergic reaction occurs.

KEEP OUT OF REACH OF CHILDREN

If swallowed, get medical help or contact a Poison Control Center right away.

DIRECTIONS

▪ Adults and children over 12 years:

▪ Apply a thin layer to affected area not more than 3–4 times daily

▪ Children under 12 years: Consult a doctor before use

▪ Wash hands after application

INACTIVE INGREDIENTS

Purified Water, Glycerin, Allantoin,Tocopheryl Acetate (Vitamin E),Carbomer, Propylene Glycol,Sodium Hydroxide, Phenoxyethanol,

Ethylhexylglycerin

OTHER INFORMATION

Store at room temperature (15–30°C / 59–86°F) Tamper evident: Do not use if seal is broken or missing.